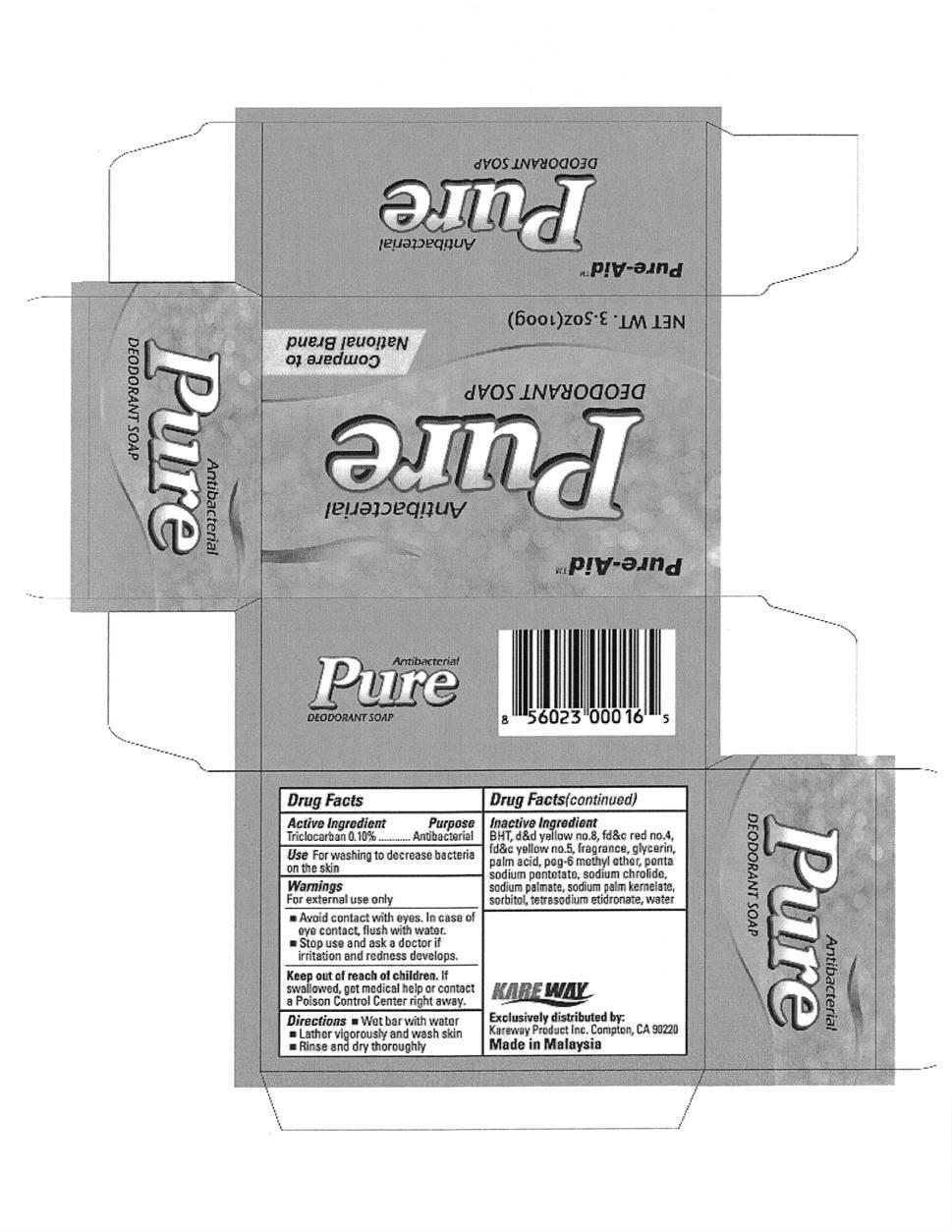 DRUG LABEL: Antibacterial Gold
NDC: 67510-0016 | Form: SOAP
Manufacturer: Kareway Product, Inc.
Category: otc | Type: HUMAN OTC DRUG LABEL
Date: 20121031

ACTIVE INGREDIENTS: TRICLOCARBAN .1 g/100 g
INACTIVE INGREDIENTS: D&C YELLOW NO. 8; FD&C RED NO. 4; FD&C YELLOW NO. 5; GLYCERIN; PALMITIC ACID; PEG-6 METHYL ETHER; PENTASODIUM PENTETATE; SODIUM CHLORIDE; SODIUM PALMITATE; SODIUM PALM KERNELATE; SORBITOL; ETIDRONATE TETRASODIUM; WATER; BUTYLATED HYDROXYTOLUENE

Drug Facts

Active Ingredient

Triclocarban 0.10%

Purpose

Antibacterial

Use

For washing to decrease bacteria on the skin

Warnings

For external use only

- Avoid contact with eyes. In case of eye contact, flush with water.
- Stop use and ask a doctor if irritation and redness develops.

Keep out of reach of children.

If swallowed, get medical help or contact a Poison Control Center right away.

Directions

- Wet bar with water
- Lather vigorously and wash skin
- Rinse and dry thoroghly

Inactive Ingredient

BHT, DC yellow no.8, FDC red no.4, FDC yellow no.5, glycerin, palmitic acid, PEG-6 methyl ether, pentasodium pentetate, sodium chloride, sodium palmitate, sodium palm kernelate, sorbitol, tetrasodium etidronate, water

Package label

Pure Antibacterial